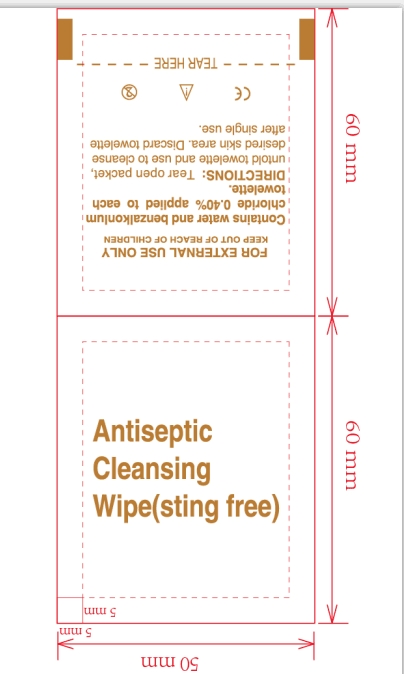 DRUG LABEL: Antiseptic Cleaning wipe
NDC: 84449-004 | Form: PATCH
Manufacturer: SHENZHEN BENLIJU BIO-TECH CO.,LTD
Category: otc | Type: HUMAN OTC DRUG LABEL
Date: 20260105

ACTIVE INGREDIENTS: BENZALKONIUM CHLORIDE 4 mg/1 g; CHLORHEXIDINE 10 mg/1 g
INACTIVE INGREDIENTS: PHENOXYETHANOL; WATER

ACTIVE INGREDIENT

benzalkonium chloride ,chlorhexidine

PURPOSE

disinfect

INDICATIONS AND USAGE

For Daily cleaning and disinfecting care wipe for human skin or object surface.

WARNINGS

*For extemal use only.
*Flammable. keep away from fire or flame.

Do not use " with electrocautery procedures " in the eyes. lf contact occurs, flush eyes with water.

When using this product keep out of eyes, ears, and mouth. In case of contact with eyes, rinse eyes thoroughly with water.

*Stop use if irritation and redness develop. If condition persists consult your health care practioner.

*Stop use and ask a doctor if irritation or rash occurs. These may be signs of a serious condition.

Keep out of reach of children. If swallowed, get medical help or contact a Poison Control Center right away.

DOSAGE AND ADMINISTRATION

For Daily cleaning and disinfecting care wipe for human skin or object surface.One piece at a time.

STORAGE AND HANDLING

Store at room temperature.

INACTIVE INGREDIENT

water,phenoxyethanol